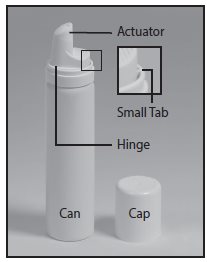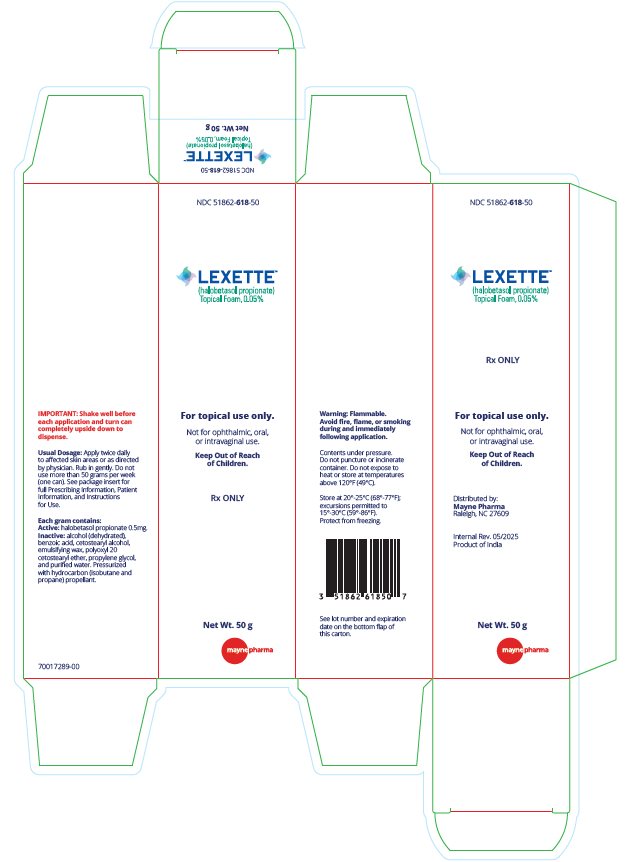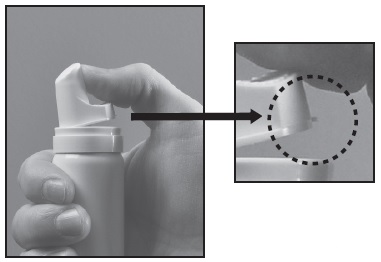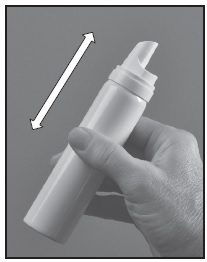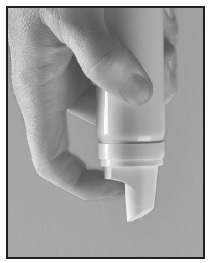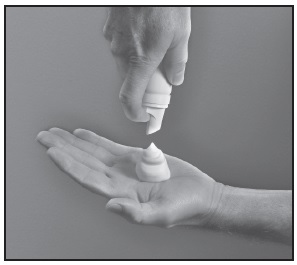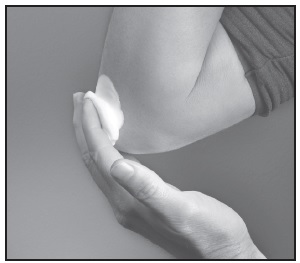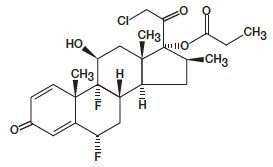 DRUG LABEL: LEXETTE
NDC: 51862-618 | Form: AEROSOL, FOAM
Manufacturer: Mayne Pharma
Category: prescription | Type: HUMAN PRESCRIPTION DRUG LABEL
Date: 20250531

ACTIVE INGREDIENTS: HALOBETASOL PROPIONATE 0.5 mg/1 g
INACTIVE INGREDIENTS: ALCOHOL; PROPYLENE GLYCOL; POLAWAX POLYSORBATE; POLYOXYL 20 CETOSTEARYL ETHER; CETOSTEARYL ALCOHOL; WATER; BENZOIC ACID

HIGHLIGHTS OF PRESCRIBING INFORMATION

These highlights do not include all the information needed to use LEXETTE safely and effectively. See full prescribing information for LEXETTE.
LEXETTE® (halobetasol propionate) topical foam
Initial U.S. Approval: 1990

1 INDICATIONS AND USAGE

LEXETTE is a corticosteroid indicated for the topical treatment of plaque psoriasis in patients twelve (12) years of age and older. (1)

2 DOSAGE AND ADMINISTRATION

- Shake before use. (2)
- Apply LEXETTE as a thin uniform film to the affected skin twice daily for up to two weeks. Rub in gently. (2)
- Do not use more than 50 grams per week. (2)
- Discontinue LEXETTE when control is achieved. (2)
- If no improvement is seen within 2 weeks, reassess diagnosis. (2)
- Treatment beyond 2 consecutive weeks is not recommended. (2)
- Do not use with occlusive dressings unless directed by a physician. (2)
- Avoid use on the face, groin, or axillae. (2)
- LEXETTE is not for ophthalmic, oral, or intravaginal use. (2)

3 DOSAGE FORMS AND STRENGTHS

Topical foam: 0.05% (0.5 mg/g). (3)

4 CONTRAINDICATIONS

None.

5 WARNINGS AND PRECAUTIONS

- Reversible hypothalamic-pituitary-adrenal (HPA) axis suppression may occur, with the potential for glucocorticosteroid insufficiency during or after treatment. (5.1)
- Systemic effects following prolonged exposure of topical corticosteroids may also include Cushing’s syndrome, hyperglycemia, and glucosuria. (5.1)
- Use of potent corticosteroids on large areas, for prolonged durations, under occlusive dressings, or on an altered skin barrier may increase systemic exposure. (5.1)
- Children may be more susceptible to systemic toxicity when treated with topical corticosteroids. (5.1, 8.4)
- Local adverse reactions with topical steroids may include atrophy, striae, irritation, acneiform eruptions, hypopigmentation, and allergic contact dermatitis. Adverse reactions may be more likely to occur with occlusive use or more potent corticosteroids. (5.2)
- Topical corticosteroids may increase the risk of cataract and glaucoma formation. If visual symptoms occur, consider referral to an ophthalmologist for evaluation. (5.3)
- Initiate appropriate therapy if concomitant skin infections develop. (5.4)
- Flammable contents. Avoid heat, flame, or smoking during and immediately following application. (5.6)

6 ADVERSE REACTIONS

The most commonly reported adverse reactions (≥1%) are application site pain and headache. (6.1)

To report SUSPECTED ADVERSE REACTIONS, contact Padagis® at 1-866-634-9120 or FDA at 1-800-FDA-1088 or www.fda.gov/medwatch.

FULL PRESCRIBING INFORMATION

1 INDICATIONS AND USAGE

LEXETTE® is indicated for the topical treatment of plaque psoriasis in patients 12 years of age and older.

2 DOSAGE AND ADMINISTRATION

Shake can prior to use and turn can completely upside down to dispense. Apply LEXETTE as a thin uniform film to the affected skin twice daily for up to two weeks. Rub in gently. Wash hands after applying the product.

Discontinue therapy when control is achieved. If no improvement is seen within two weeks, reassessment of the diagnosis may be necessary.

Treatment beyond two weeks is not recommended and the total dosage should not exceed 50 grams per week because of the potential for the drug to suppress the hypothalamic-pituitary-adrenal (HPA) axis [see Warnings and Precautions (5.1)]. Do not use with occlusive dressings unless directed by a physician.

Avoid use on the face, groin, or axillae.

Avoid contact with eyes. Wash hands after each application, unless it is for treatment of the hands.

LEXETTE is for topical use only.

LEXETTE is not for ophthalmic, oral, or intravaginal use.

3 DOSAGE FORMS AND STRENGTHS

LEXETTE® (halobetasol propionate) topical foam is a white to off-white topical foam. Each gram of LEXETTE, 0.05% contains 0.5 mg of halobetasol propionate.

4 CONTRAINDICATIONS

None.

5 WARNINGS AND PRECAUTIONS

5.1 Hypothalamic-Pituitary-Adrenal (HPA) Axis Suppression and Other Adverse Endocrine Effects

LEXETTE is a topical corticosteroid that has been shown to suppress the hypothalamic-pituitary-adrenal (HPA) axis.

Systemic effects of topical corticosteroids may include reversible HPA axis suppression, with the potential for glucocorticosteroid insufficiency. This may occur during treatment or upon withdrawal of treatment of the topical corticosteroid. The potential for hypothalamic-pituitary-adrenal (HPA) suppression with LEXETTE was evaluated in the following studies:

- In a study of 25 adult subjects with moderate to severe plaque psoriasis involving ≥15% of their body surface area. LEXETTE produced laboratory evidence of HPA axis suppression when used twice daily for two weeks in 6 out of 25 (24%) adult subjects with plaque psoriasis. All subjects returned to normal HPA axis function at follow-up at least 4 weeks after stopping the treatment [see Clinical Pharmacology (12.2)].
- In another clinical study, 24 subjects 12 to less than 18 years old with stable plaque psoriasis involving 10% or more of their body surface area applied LEXETTE to affected areas twice daily for two weeks. Of the 23 subjects evaluated for HPA axis suppression, laboratory evidence of adrenal suppression occurred in 6 subjects (26.1%), whom recovered upon retesting after at least 4 weeks of stopping the treatment [see Clinical Pharmacology (12.2)].

Because of the potential for systemic absorption, use of topical corticosteroids, including LEXETTE, may require that patients be evaluated periodically for evidence of HPA axis suppression. Factors that predispose a patient using a topical corticosteroid to HPA axis suppression include the use of more potent corticosteroids, use over large surface areas, prolonged use, occlusive use, use on an altered skin barrier, concomitant use of multiple corticosteroid-containing products, liver failure, and young age. An ACTH stimulation test may be helpful in evaluating patients for HPA axis suppression.

If HPA axis suppression is documented, attempt to gradually withdraw the drug, reduce the frequency of application, or substitute a less potent steroid. Manifestations of adrenal insufficiency may require supplemental systemic corticosteroids. Recovery of HPA axis function is generally prompt and complete upon discontinuation of topical corticosteroids.

Systemic effects of topical corticosteroids may also include Cushing's syndrome, hyperglycemia, and glucosuria. Use of more than one corticosteroid-containing product at the same time may increase the total systemic exposure to topical corticosteroids.

Pediatric patients may be more susceptible than adults to systemic toxicity from the use of topical corticosteroids due to their larger surface-to-body mass ratios [see Use in Specific Populations (8.4)].

5.2 Local Adverse Reactions

Local adverse reactions from topical corticosteroids may include atrophy, striae, telangiectasias, burning, itching, irritation, dryness, folliculitis, acneiform eruptions, hypopigmentation, perioral dermatitis, allergic contact dermatitis, secondary infection, and miliaria. These may be more likely to occur with occlusive use, prolonged use, or use of higher potency corticosteroids, including LEXETTE. Some local adverse reactions may be irreversible.

5.3 Ophthalmic Adverse Reactions

Use of topical corticosteroids may increase the risk of posterior subcapsular cataracts and glaucoma. Cataracts and glaucoma have been reported in postmarketing experience with the use of topical corticosteroid products.

Advise patients to report any visual symptoms and consider referral to an ophthalmologist for evaluation.

5.4 Concomitant Skin Infections

Use an appropriate antimicrobial agent if a skin infection is present or develops. If a favorable response does not occur promptly, discontinue use of LEXETTE until the infection has been adequately treated.

5.5 Allergic Contact Dermatitis

Allergic contact dermatitis with corticosteroids is usually diagnosed by observing failure to heal rather than noting a clinical exacerbation. Consider confirmation of a clinical diagnosis of allergic contact dermatitis by appropriate patch testing. Discontinue LEXETTE if allergic contact dermatitis is established.

5.6 Flammability

LEXETTE is flammable. Avoid fire, flame, or smoking during and immediately following application.

6 ADVERSE REACTIONS

The following adverse reactions are discussed in greater detail in other sections of the label:

- Hypothalamic-Pituitary-Adrenal (HPA) Axis Suppression and Other Adverse Endocrine Effects [see Warnings and Precautions (5.1)]
- Allergic Contact Dermatitis [see Warnings and Precautions (5.5)]

6.1 Clinical Trials Experience

Because clinical trials are conducted under widely varying conditions, adverse reaction rates observed in the clinical trials of a drug cannot be directly compared to rates in the clinical trials of another drug and may not reflect the rates observed in practice.

In randomized, multicenter, vehicle-controlled clinical trials, 351 adults with plaque psoriasis were treated with LEXETTE twice daily for up to two weeks (up to approximately 50 grams per week). Table 1 presents selected adverse reactions that occurred in at least 1% of subjects.

Table 1: Adverse Reactions Occurring in ≥ 1% of Subjects through Week 2
 | HBP Foam; N=351 | Vehicle Foam; N=353
Adverse Reaction | % | %
Application site burning/stinging | 12% | 15%
Application site pain | 1% | <1%
Headache | 1% | <1%

Skin atrophy (n=1) and telangiectasia (n=2) were reported with LEXETTE, but not with vehicle foam.

6.2 Postmarketing Experience

Because the reactions are reported voluntarily from a population of uncertain size, it is not always possible to reliably estimate their frequency or establish a causal relationship to drug exposure.

The following local adverse reactions have been reported with topical corticosteroids: folliculitis, acneiform eruptions, hypopigmentation, perioral dermatitis, allergic contact dermatitis, secondary infection, irritation, striae, and miliaria. They may occur more frequently with the use of occlusive dressings and higher potency corticosteroids, such as halobetasol propionate.

8 USE IN SPECIFIC POPULATIONS

8.1 Pregnancy

Risk Summary

There are no available data on LEXETTE use in pregnant women to inform a drug-associated risk for adverse developmental outcomes. In animal reproduction studies, increased malformations, including cleft palate and omphalocele, were observed after oral administration of halobetasol propionate during organogenesis to pregnant rats and rabbits. No comparisons of animal exposure with human exposure may be calculated due to minimal systemic exposure in humans after topical administration of LEXETTE [see Clinical Pharmacology (12.3)].

The background risk of major birth defects and miscarriage for the indicated population are unknown. In the U.S. general population, the estimated background risk of major birth defects and miscarriage in clinically recognized pregnancies is 2-4% and 15-20%, respectively.

Data

Animal Data

Halobetasol propionate has been shown to cause malformations in rats and rabbits when given orally during organogenesis at doses of 0.04 to 0.1 mg/kg/day in rats and 0.01 mg/kg/day in rabbits. Halobetasol propionate was embryotoxic in rabbits, but not in rats. Cleft palate was observed in both rats and rabbits. Omphalocele was seen in rats, but not in rabbits.

8.2 Lactation

Risk Summary

There are no data on the presence of halobetasol propionate or its metabolites in human milk, the effects on the breastfed infant, or the effects on milk production after topical application to women who are breastfeeding.

Systemically administered corticosteroids appear in human milk and could suppress growth, interfere with endogenous corticosteroid production, or cause other untoward effects. It is not known whether topical administration of corticosteroids could result in sufficient systemic absorption to produce detectable quantities in human milk.

The developmental and health benefits of breastfeeding should be considered along with the mother’s clinical need for LEXETTE and any potential adverse effects on the breastfed infant from LEXETTE or from the underlying maternal condition.

Clinical Considerations

Advise breastfeeding women not to apply LEXETTE directly to the nipple and/or areola to avoid direct infant exposure.

8.4 Pediatric Use

Safety and effectiveness of LEXETTE in patients younger than 12 years of age have not been established; therefore, use in children younger than 12 years is not recommended.

The safety and effectiveness of LEXETTE for the treatment of stable plaque psoriasis in subjects 12 to less than 18 years of age is supported by evidence from adequate and well-controlled studies in adults and from one open-label safety study in 24 subjects aged 12 to less than 18 years. Subjects 12 to less than 18 years with stable plaque psoriasis covering a minimum of 10% of the total body surface area at baseline were treated twice daily for 2 weeks with LEXETTE. Hypothalamic-pituitary-adrenal (HPA) axis function (ACTH stimulation test) was evaluated in a subset of 23 subjects. After 2 weeks of treatment, 6 of 23 subjects (26.1%) experienced laboratory evidence of adrenal suppression (i.e., cortisol serum level of ≤18 μg/dL) that recovered upon retesting after at least 4 weeks of stopping the treatment [see Clinical Pharmacology (12.2)].

Because of higher skin surface area to body mass ratios, pediatric patients are at a greater risk than adults of HPA axis suppression and Cushing’s syndrome when they are treated with topical corticosteroids. They are therefore also at greater risk of adrenal insufficiency during or after withdrawal of treatment. Adverse reactions including striae have been reported with use of topical corticosteroids in infants and children [see Warnings and Precautions (5.1)].

HPA axis suppression, Cushing’s syndrome, linear growth retardation, delayed weight gain, and intracranial hypertension have been reported in children receiving topical corticosteroids. Manifestations of adrenal suppression in children include low plasma cortisol levels and an absence of response to ACTH stimulation. Manifestations of intracranial hypertension include bulging fontanelles, headaches, and bilateral papilledema [see Warnings and Precautions (5.1)].

8.5 Geriatric Use

Clinical studies with LEXETTE included 131 patients aged 65 years and over. No overall differences in safety or effectiveness were observed between these patients and those younger than 65 years.

10 OVERDOSAGE

Topically applied LEXETTE can be absorbed in sufficient amounts to produce systemic effects [see Warnings and Precautions (5.1)].

11 DESCRIPTION

LEXETTE is a hydroethanolic aerosol foam that contains a corticosteroid, halobetasol propionate. The chemical name of halobetasol propionate is 21-chloro-6α, 9-difluoro-11β, 17-dihydroxy-16β-methylpregna-1, 4-diene-3,20-dione 17-propionate. Halobetasol propionate is a white to off-white crystalline powder with a molecular weight of 484.96 and a molecular formula of C25H31ClF2O5. It has the following structural formula:

It is practically insoluble in water and freely soluble in dichloromethane and in acetone. Each gram of LEXETTE contains 0.5 mg of halobetasol propionate in a white to off-white foam base consisting of alcohol (dehydrated), benzoic acid, cetostearyl alcohol, emulsifying wax, polyoxyl 20 cetostearyl ether, propylene glycol and purified water. LEXETTE is dispensed from an aluminum can pressurized with a hydrocarbon (isobutane and propane) propellant.

12 CLINICAL PHARMACOLOGY

12.1 Mechanism of Action

Corticosteroids play a role in cellular signaling, immune function, inflammation, and protein regulation; however, the precise mechanism of action in plaque psoriasis is unknown.

12.2 Pharmacodynamics

Vasoconstrictor Assay

A vasoconstrictor assay in healthy patients with LEXETTE indicated that the formulation is in the super-high range of potency as compared to other topical corticosteroids; however, similar blanching scores do not necessarily imply therapeutic equivalence.

Hypothalamic-pituitary-adrenal (HPA) axis suppression

The potential for hypothalamic-pituitary-adrenal axis (HPA-axis) suppression was evaluated in the following two studies. In both studies, the criteria for HPA-axis suppression was a serum cortisol level of less than or equal to 18 micrograms per deciliter 30 minutes after stimulation with cosyntropin (adrenocorticotropic hormone, ACTH).

In the first study, LEXETTE was applied to 25 adult subjects with moderate to severe plaque psoriasis involving a mean body surface area of 18.4%. A mean dose of 3.7 g of LEXETTE was applied twice daily for two weeks and produced laboratory evidence of HPA axis suppression in 6 of 25 (24%) subjects. All subjects returned to normal HPA axis function at follow-up at least 4 weeks after stopping the treatment.

In the second study, LEXETTE was applied to 24 subjects 12 to less than 18 years of age with stable plaque psoriasis with a mean percent BSA of 15.1% (range of 11% to 23%). The mean dose of LEXETTE used was 3.1 grams, which was applied twice daily for two weeks. In the study, 24 subjects completed the study, and 23 subjects had evaluable ACTH stimulation tests. HPA axis suppression was observed in 6 of the 23 subjects (26.1%), and all subjects returned to normal HPA axis function at follow-up at least 4 weeks after stopping the treatment.

12.3 Pharmacokinetics

The extent of percutaneous absorption of topical corticosteroids is determined by many factors, including the vehicle, the integrity of the epidermal barrier, and the use of occlusive dressings. Topical corticosteroids can be absorbed from normal intact skin. Inflammation and/or other disease processes in the skin may increase percutaneous absorption.

In the HPA-axis and pharmacokinetic study, as described above in Clinical Pharmacology (12.2), pharmacokinetics was evaluated in a subgroup of 23 adult subjects with moderate to severe plaque psoriasis following twice daily treatment for 14 days. Plasma concentration of halobetasol propionate (HBP) was measurable in all subjects and steady state was achieved by Day 14. The mean (± standard deviation) Cmax concentration for HBP on Day 14 was 199.7 ± 217.3 pg/mL, with the corresponding median Tmax value of 1 hour (range 0 – 12 hours); mean area under the halobetasol propionate concentration versus time curve over the dosing interval (AUCt) was 1434.9 ± 1310.6 pg•h/mL.

In the HPA axis study in subjects 12 to less than 18 years [see Clinical Pharmacology (12.2)], trough plasma concentrations of HBP were measured on Day 8 and Day 15 in 23 subjects following twice daily treatment for 14 days. On Day 8, nine (9) of the 23 evaluable subjects had morning trough concentrations of halobetasol propionate in plasma that were above the quantifiable limit (≥20.0 pg/mL); mean halobetasol concentration was 154.6 ± 308.67 pg/mL. Similarly, on Day 15, nine (9) of the 23 evaluable subjects had morning trough concentrations of halobetasol propionate above the quantifiable limit; mean halobetasol concentration was 59.9 ± 90.15 pg/mL. Of the 9 subjects with quantifiable plasma concentrations at Day 15, seven (7) also had quantifiable plasma concentrations at Day 8.

13 NONCLINICAL TOXICOLOGY

13.1 Carcinogenesis, Mutagenesis, Impairment of Fertility

Long-term animal studies have not been performed to evaluate the carcinogenic potential of halobetasol propionate.

In a 90-day repeat-dose toxicity study in rats, topical administration of LEXETTE at dose concentrations from 0.005% to 0.05% or from 0.011 to 0.11 mg/kg/day of halobetasol propionate resulted in a toxicity profile consistent with long-term exposure to corticosteroids including adrenal atrophy, histopathological changes in several organ systems indicative of severe immune suppression, and opportunistic fungal and bacterial infections. A no observable adverse effect level could not be determined in this study. Although the clinical relevance of the findings in animals to humans is not clear, sustained glucocorticoid-related immune suppression may increase the risk of infection and possibly the risk of carcinogenesis.

Halobetasol propionate was not found to be genotoxic in the Ames/Salmonella assay, in the Chinese hamster CHO/HGPRT assay, in the mouse micronucleus test, in the sister chromatid exchange test in somatic cells of the Chinese hamster, or in the chromosome aberration test in somatic cells of Chinese hamsters. Positive mutagenicity effects were observed in two genotoxicity assays: Chinese hamster nuclear anomaly test and mouse lymphoma gene mutation assay in vitro. Studies in the rat following oral administration at dose levels up to 0.05 mg/kg/day indicated no impairment of fertility or general reproductive performance.

14 CLINICAL STUDIES

LEXETTE was evaluated for the treatment of moderate to severe plaque psoriasis in two multicenter, randomized, double-blind, vehicle-controlled studies (Study 1 [NCT02368210] and Study 2 [NCT02742441]).

These studies were conducted in 560 subjects 18 years of age and older with plaque psoriasis involving between 2% and 12% body surface area. Baseline disease severity was determined using a static, five-level Investigator’s Global Assessment (IGA) scale, on which a subject scored either moderate or severe. Overall, approximately 60% of subjects were male and approximately 90% were Caucasian.

Subjects applied LEXETTE or vehicle to all affected areas twice daily for up to 14 consecutive days. The primary measure of efficacy was Overall Treatment Success, defined as the proportion of subjects who were cleared or almost cleared with at least a two-grade improvement from baseline at Week 2 (end of treatment) based on the IGA. The studies also evaluated treatment success for the individual signs of psoriasis (plaque elevation, scaling, and erythema) at the end of treatment. Table 2 presents these results.

Table 2: Efficacy Results at Week 2 in Subjects with Plaque Psoriasis
 | Study 1 |  | Study 2
 | LEXETTE; N=75 | Vehicle Foam; N=76 | LEXETTE; N=205 | Vehicle Foam; N=204
Overall Treatment Success [Subjects whose condition was cleared or almost cleared of all signs of psoriasis and with at least a two-grade improvement from baseline based on the IGA.] | 19 (25%) | 3 (4%) | 63 (31%) | 15 (7%)
Plaque Elevation [Subjects who were cleared or almost cleared of the designated clinical sign with at least a two-grade improvement from baseline. Individual signs were rated by severity using a five-point scale ranging from 0 (clear) to 4 (severe). Subjects with baseline value of 0 or 1 were excluded.] | 20/75 (27%) | 3/76 (4%) | 71/202 (35%) | 20/203 (10%)
Scaling | 21/75 (28%) | 4/76 (5%) | 68/201 (34%) | 20/204 (10%)
Erythema | 16/75 (21%) | 2/76 (3%) | 59/205 (29%) | 17/204 (8%)

16 HOW SUPPLIED/STORAGE AND HANDLING

16.1 How Supplied

LEXETTE (halobetasol propionate) topical foam, 0.05% is a white to off-white foam.

It is supplied in aluminum cans of:
50 grams (NDC 51862-618-50)

16.2 Storage

Store at 20°-25°C (68°-77°F); excursions permitted to 15ºC and 30ºC (59ºF to 86ºF). Contents under pressure.

Do not puncture or incinerate. Do not expose to heat or store at temperatures above 120°F (49°C).

Do not freeze.

16.3 Handling

LEXETTE is flammable; avoid heat, flame, or smoking when using this product.

17 PATIENT COUNSELING INFORMATION

Advise the patient to read the FDA-approved patient labeling (Patient Information and Instructions for Use).

This information is intended to aid in the safe and effective use of this medication. It is not a disclosure of all administration instructions or all possible adverse or unintended effects. Inform patients of the following:

Important Administration Instructions:

- Total dosage should not exceed 50 grams (one can) per week [see Dosage and Administration (2)].
- Advise patients to avoid use on the face, groin, or axillae. Avoid contact with eyes [see Dosage and Administration (2)].
- Inform patients that topical corticosteroids may cause HPA axis suppression and local adverse reactions [see Warnings and Precautions (5.1)].
- Breastfeeding women should not apply LEXETTE directly to the nipple and/or areola to avoid direct exposure to the infant [see Use in Specific Populations (8.2)].
- This product is flammable; avoid heat, flame, or smoking during and immediately following application of this product.

Rx Only

Distributed by:
Mayne Pharma
Raleigh, NC 27609

Rev 05/2025

Patient Package Insert

PATIENT INFORMATION

LEXETTE® (lex-et)

(halobetasol propionate)

Topical Foam, 0.05%

Important: LEXETTE is for use on the skin only. Do not apply LEXETTE near or in your eyes, mouth, or vagina.

What is LEXETTE?

LEXETTE is a prescription corticosteroid medicine used on the skin to treat plaque psoriasis in people 12 years of age and older.

It is not known if LEXETTE is safe and effective in children under 12 years of age.

Before using LEXETTE, tell your healthcare provider about all of your medical conditions, including if you:

• have had irritation or other skin reaction to a steroid medicine in the past.

• have a skin infection. You may need medicine to treat the skin infection before using LEXETTE.

• have diabetes.

• have adrenal gland problems.

• have liver problems.

• plan to have surgery.

• are pregnant or plan to become pregnant. It is not known if LEXETTE will harm your unborn baby.

• are breastfeeding or plan to breastfeed. It is not known if halobetasol propionate passes into your breast milk. If you use LEXETTE and breastfeed, do not apply LEXETTE to your nipple or areola to avoid getting LEXETTE into your baby’s mouth.

Tell your healthcare provider about all the medicines you take, including prescription and over-the-counter medicines, vitamins, and herbal supplements. Especially tell your healthcare provider if you take other corticosteroid medicines by mouth, or injection, or use other products on your skin that contain corticosteroid.

How should I use LEXETTE?

See the “Instructions for Use” for detailed information about the right way to apply LEXETTE.

• Use LEXETTE exactly as your healthcare provider tells you to use it.

• Apply a thin layer of LEXETTE to the affected skin areas 2 times each day.

• You should not use more than 50 grams of LEXETTE in 1 week.

• Avoid using LEXETTE on your face, underarms (armpits), or groin areas.

• Do not bandage, cover, or wrap the treated skin area unless your healthcare provider tells you to.

• Talk to your healthcare provider if your skin does not improve after 2 weeks of treatment with LEXETTE.

• Do not use LEXETTE longer than 2 continuous weeks unless advised to do so by your prescriber.

• Wash your hands after using LEXETTE unless you are using the medicine to treat your hands.

What should I avoid while using LEXETTE?

LEXETTE is flammable. Avoid heat, flame, or smoking during and right after applying LEXETTE to your skin.

What are the possible side effects of LEXETTE?

LEXETTE may cause serious side effects, including:

• LEXETTE can pass through your skin. Too much LEXETTE passing through your skin can cause adrenal glands to stop working.

• Cushing’s syndrome, a condition that happens when your body is exposed to too much of the hormone cortisol.

• High blood sugar (hyperglycemia).

• Vision problems. LEXETTE may increase your chance of developing cataract(s) and glaucoma. Tell your healthcare provider if you develop blurred vision or other vision problems during treatment with LEXETTE.

• Skin reactions at the treated skin site. Tell your healthcare provider if you get any skin reactions or skin infections.

• Effects on growth and weight in children.

Your healthcare provider may do certain blood tests to check for side effects.

The most common side effect of LEXETTE is mild to moderate pain at the treated site. These are not all of the possible side effects of LEXETTE.

Call your doctor for medical advice about side effects. You may report side effects to FDA at 1-800-FDA-1088.

How should I store LEXETTE?

• Store LEXETTE at room temperature between 68°F to 77°F (20°C to 25°C).

• Do not puncture or burn LEXETTE can.

• Do not store LEXETTE next to heat or store at temperatures above 120°F (49°C).

• Do not freeze LEXETTE.

Keep LEXETTE and all medicines out of the reach of children.

General information about the safe and effective use of LEXETTE.

Medicines are sometimes prescribed for purposes other than those listed in a Patient Information leaflet. Do not use LEXETTE for a condition for which it was not prescribed. Do not give LEXETTE to other people, even if they have the same symptoms that you have. It may harm them. You can ask your pharmacist or healthcare provider for information about LEXETTE that is written for health professionals.

What are the ingredients in LEXETTE?

Active ingredient: halobetasol propionate

Inactive ingredients: alcohol (dehydrated), benzoic acid, cetostearyl alcohol, emulsifying wax, polyoxyl 20 cetostearyl ether, propylene glycol, and purified water.

LEXETTE is dispensed from an aluminum can pressurized with a hydrocarbon propellant containing isobutane and propane.

Distributed by:
Mayne Pharma
Raleigh, NC 27609

For more information, call 1-866-634-9120

This Patient Information has been approved by the U.S. Food and Drug Administration.

Revised: 05/2025

Instructions for Use

LEXETTE® (lex-et)

(halobetasol propionate) Topical Foam, 0.05%

Read the Patient Information and Instructions for Use before you use LEXETTE.

Important information: LEXETTE is for skin use only. Do not get LEXETTE in your mouth, eyes, or vagina.

Parts of the LEXETTE can:

Step 1: Before applying LEXETTE for the first time, remove cap and break the small tab at the base of the actuator by gently pushing the actuator away from the tab as shown. Do not break the hinge on the actuator.

Step 2: Shake the can well before use.

Step 3: Turn the can completely upside down.

Step 4: Press down on the actuator to dispense a small amount of the foam into the palm of your hand.

Step 5: Apply a thin layer of LEXETTE to the affected skin area. Gently rub LEXETTE into the affected skin until the foam disappears.

Repeat Steps 4 and 5 to all the affected areas as prescribed by your healthcare provider.

Step 6: After applying LEXETTE, put the cap back on the can.

Step 7: Wash your hands after applying LEXETTE unless you are using the medicine to treat your hands.

This Instructions for Use has been approved by the U.S. Food and Drug Administration.

Distributed by:
Mayne Pharma
Raleigh, NC 27609

Rev 05/2025

70017288-00

PACKAGE/LABEL PRINCIPAL DISPLAY PANEL

NDC 51862-618-50

LEXETTE

(halobetasol propionate)

Topical Foam, 0.05%

For topical use only.

Not for ophthalmic, oral, or intravaginal use.

Keep Out of Reach of Children.

Rx ONLY

Net Wt. 50 g

mayne pharma